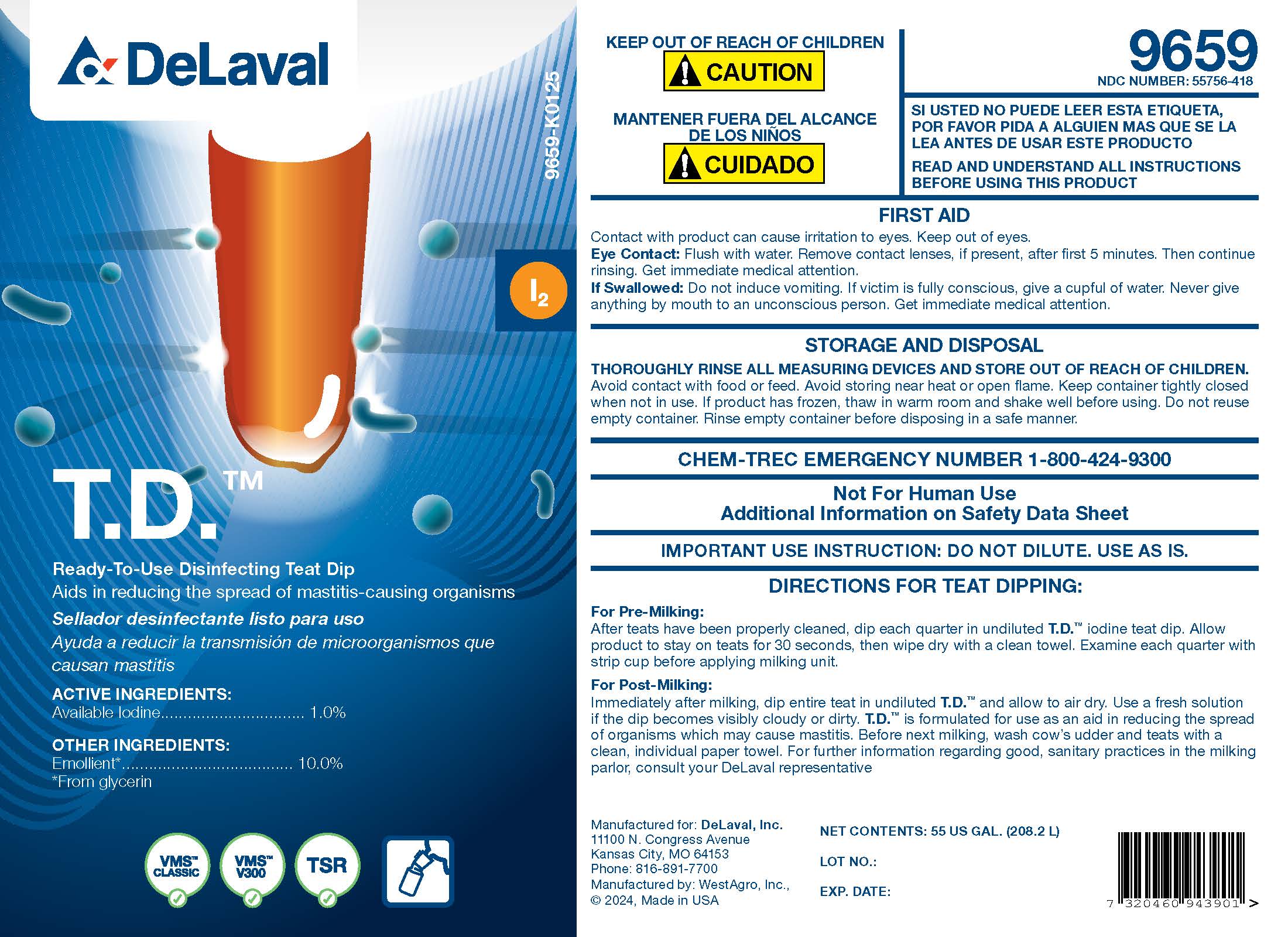 DRUG LABEL: T.D.
NDC: 55756-418 | Form: SOLUTION
Manufacturer: DeLaval, Inc.
Category: animal | Type: OTC ANIMAL DRUG LABEL
Date: 20250307

ACTIVE INGREDIENTS: IODINE 11.0 g/1 L
INACTIVE INGREDIENTS: SODIUM HYDROXIDE; ANHYDROUS CITRIC ACID; GLYCERIN; XANTHAN GUM; POLOXAMER 335; SODIUM IODIDE; NONOXYNOL-12; WATER

DeLaval
T.D.

PURPOSE

T.D.™

Aids in reducing the spread of mastitis-causing organisms

ACTIVE INGREDIENTS:

Available Iodine ............................ 1.0%

OTHER INGREDIENTS:

Emollient* ......................10.0%

*From glycerin

KEEP OUT OF REACH OF CHILDREN

! CAUTION

WARNINGS AND PRECAUTIONS

READ AND UNDERSTAND ALL INSTRUCTIONS BEFORE USING THIS PRODUCT

FIRST AID

Contact with product can cause irritation to eyes. Keep out of eyes.

Eye Contact: Flush with water. Remove contact lenses, if present, after first 5 minutes. Then continue rinsing. Get immediate medical attention.

If Swallowed: Do not induce vomiting. If victim is fully conscious, give a cupful of water. Never give anything by mouth to an unconscious person. Get immediate medical attention.

STORAGE AND DISPOSAL

THOROUGHLY RINSE ALL MEASURING DEVICES AND STORE OUT OF REACH OF CHILDREN. Avoid contact with food or feed. Avoid storing near heat or open flame. Keep container tightly closed when not in use. If product has frozen, thaw in warm room and shake well before using. Do not reuse empty container. Rinse empty container before disposing in a safe manner.

CHEM-TREC EMERGENCY NUMBER 1-800-424-9300

WARNINGS

Not For Human Use

Additional Information on Safety Data Sheet

INDICATIONS AND USAGE

IMPORTANT USE INSTRUCTION: DO NOT DILUTE. USE AS IS.

DIRECTIONS FOR TEAT DIPPING:

For Pre-Milking:

After teats have been properly cleaned, dip each quarter in undiluted T.D.™ iodine teat dip. Allow product to stay on teats for 30 seconds, then wipe dry with a clean towel. Examine each quarter with strip cup before applying milking unit.

For Post-Milking:

Immediately after milking, dip entire teat in undiluted T.D.™ and allow to air dry. Use a fresh solution if the dip becomes visibly cloudy or dirty. T.D.™ is formulated for use as an aid in reducing the spread of organisms which may cause mastitis. Before next milking, wash cow's udder and teats with a clean, individual paper towel. For further information regarding good, sanitary practices in the milking parlor, consult your DeLaval representative.

PACKAGE LABEL

Add image transcription here...